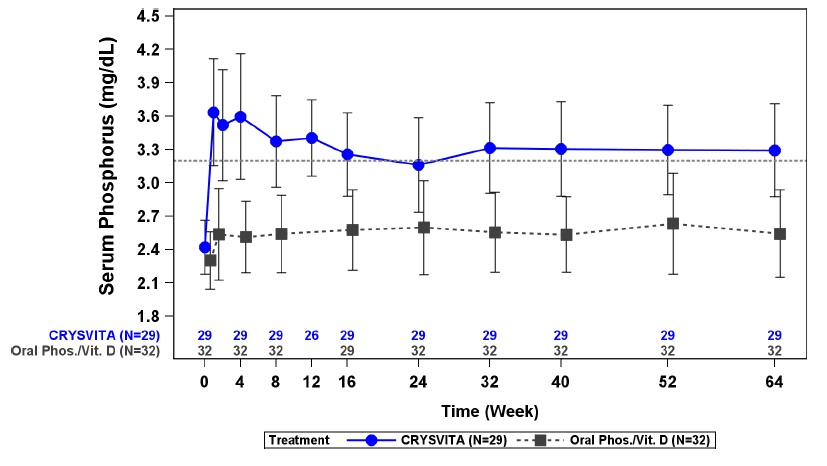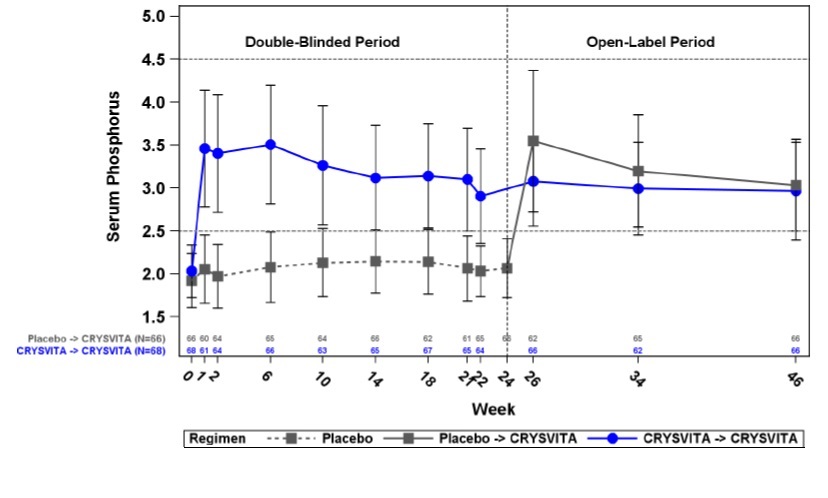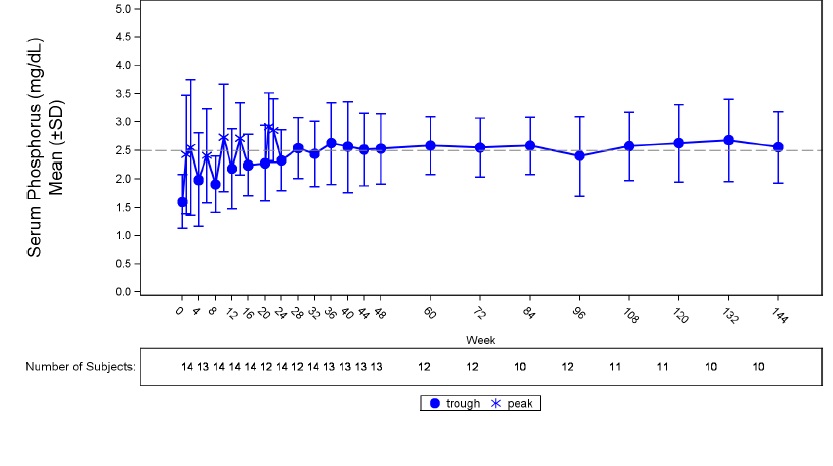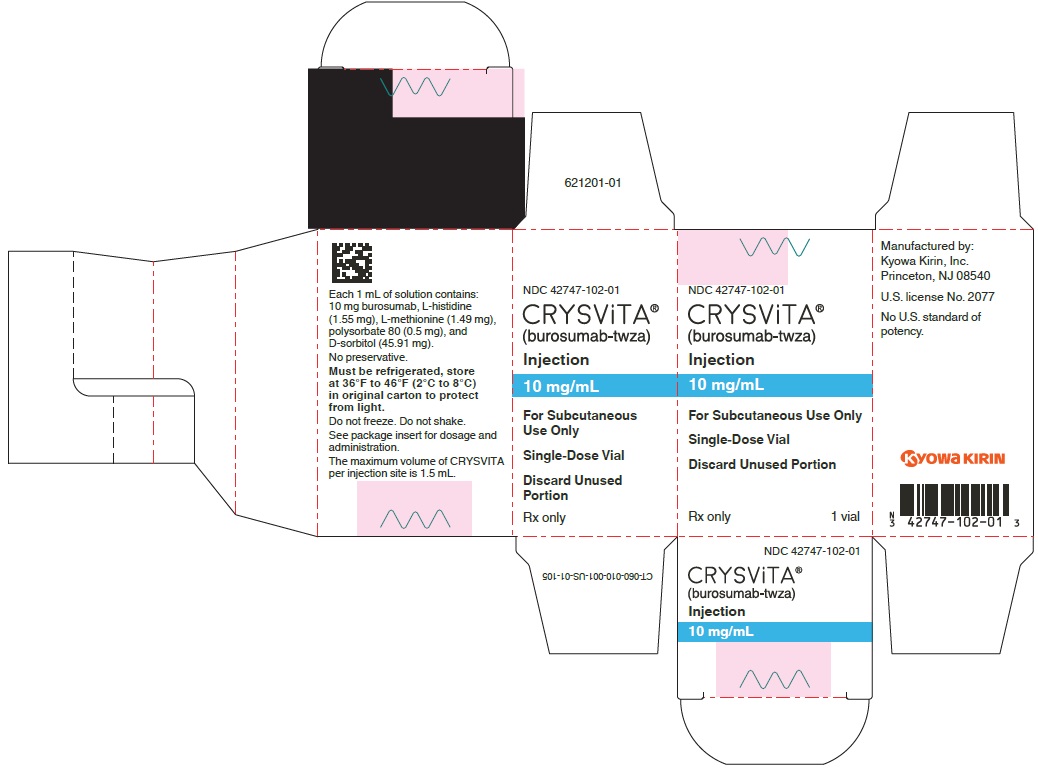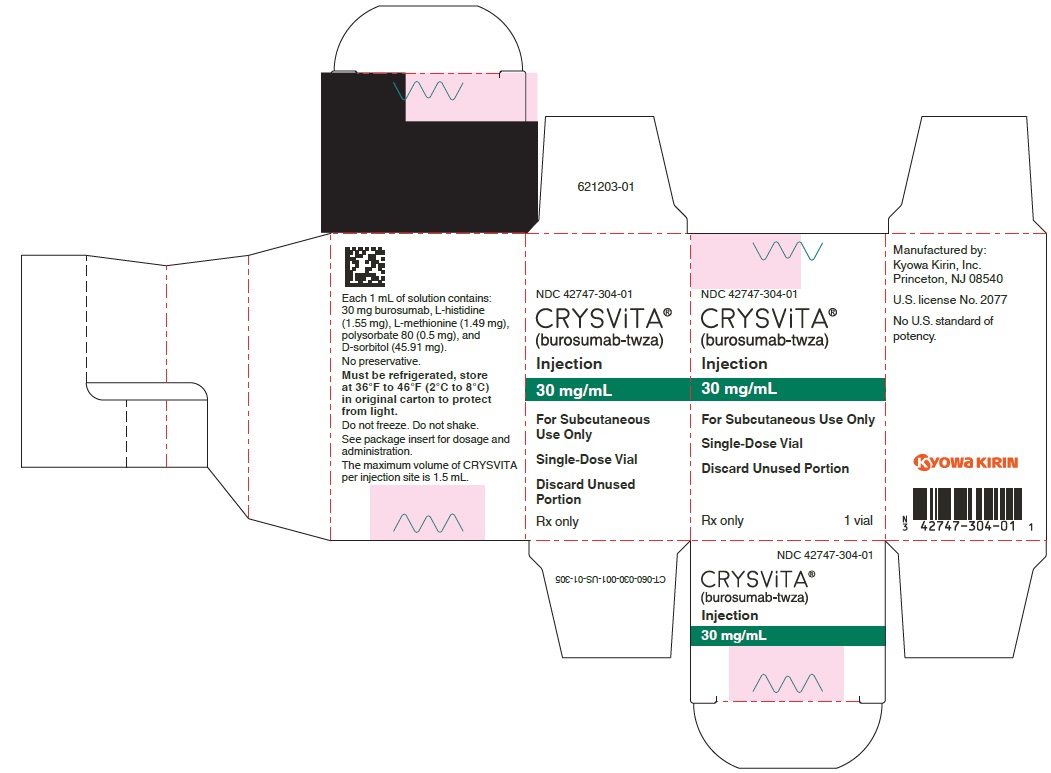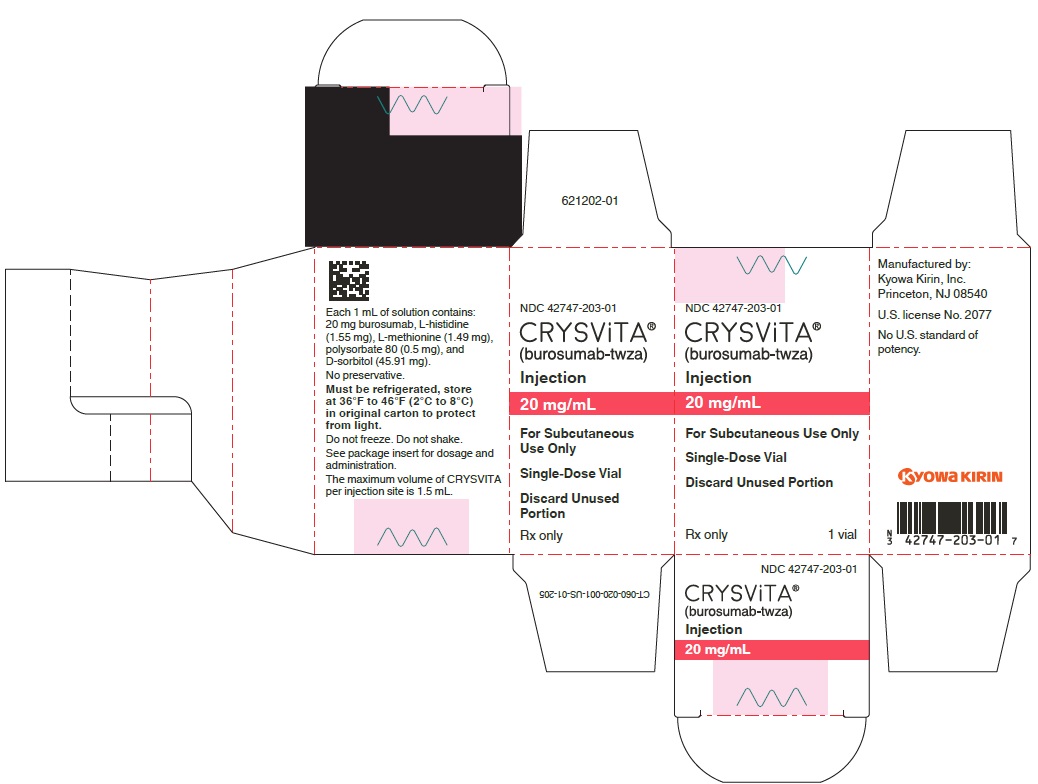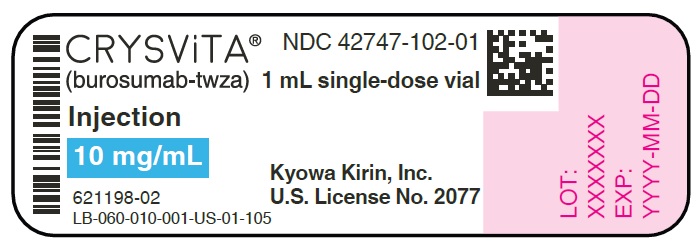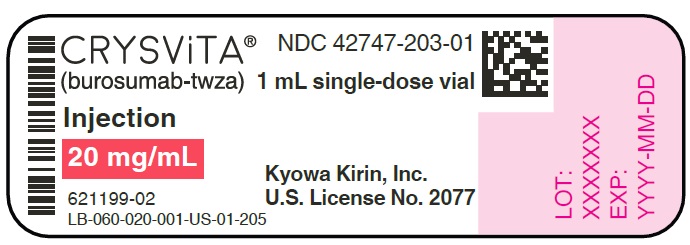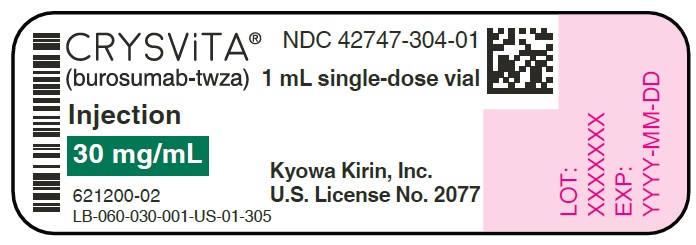 DRUG LABEL: CRYSVITA
NDC: 42747-102 | Form: INJECTION
Manufacturer: Kyowa Kirin, Inc.
Category: prescription | Type: HUMAN PRESCRIPTION DRUG LABEL
Date: 20250904

ACTIVE INGREDIENTS: BUROSUMAB 10 mg/1 mL
INACTIVE INGREDIENTS: SORBITOL 45.91 mg/1 mL; HISTIDINE 1.55 mg/1 mL; METHIONINE 1.49 mg/1 mL; POLYSORBATE 80 0.50 mg/1 mL; WATER

HIGHLIGHTS OF PRESCRIBING INFORMATION

These highlights do not include all the information needed to use CRYSVITA safely and effectively. See full prescribing information for CRYSVITA.
CRYSVITA® (burosumab-twza) injection, for subcutaneous use
Initial U.S. Approval: 2018

RECENT MAJOR CHANGES

Warnings and Precautions, Hypercalcemia (5.3) | 8/2025

1 INDICATIONS AND USAGE

CRYSVITA is a fibroblast growth factor 23 (FGF23) blocking antibody indicated for:

- The treatment of X-linked hypophosphatemia (XLH) in adult and pediatric patients 6 months of age and older. (1.1)
- The treatment of FGF23-related hypophosphatemia in tumor-induced osteomalacia (TIO) associated with phosphaturic mesenchymal tumors that cannot be curatively resected or localized in adult and pediatric patients 2 years of age and older. (1.2)

2 DOSAGE AND ADMINISTRATION

- For subcutaneous use only (2)
- Prior to starting CRYSVITA, discontinue oral phosphate and/or active vitamin D analogs for one week (2.1)
- Pediatric XLH (6 months and older):
  - For patients who weigh less than 10 kg, starting dose regimen is 1 mg/kg of body weight rounded to the nearest 1 mg, administered every two weeks (2.2)
  - For patients who weigh 10 kg and greater, starting dose regimen is 0.8 mg/kg of body weight rounded to the nearest 10 mg, administered every two weeks. The minimum starting dose is 10 mg up to a maximum dose of 90 mg. (2.2)
  Dose may be increased up to approximately 2 mg/kg (maximum 90 mg), administered every two weeks to achieve normal serum phosphorus. (2.2)
- Adult XLH: Dose regimen is 1 mg/kg body weight rounded to the nearest 10 mg up to a maximum dose of 90 mg administered every four weeks. (2.3)
- Pediatric TIO (2 years and older): Starting dose is 0.4 mg/kg of body weight rounded to the nearest 10 mg every 2 weeks. Dose may be increased up to 2 mg/kg not to exceed 180 mg, administered every two weeks. (2.4)
- Adult TIO: Starting dose is 0.5 mg/kg every four weeks. Dose may be increased up to 2 mg/kg not to exceed 180 mg, administered every two weeks. (2.5)

3 DOSAGE FORMS AND STRENGTHS

Injection: 10 mg/mL, 20 mg/mL, or 30 mg/mL in a single-dose vial (3)

4 CONTRAINDICATIONS

- With oral phosphate and/or active vitamin D analogs. (4)
- When serum phosphorus is within or above the normal range for age. (4)
- In patients with severe renal impairment or end stage renal disease. (4)

5 WARNINGS AND PRECAUTIONS

- Hypersensitivity: Discontinue CRYSVITA if serious hypersensitivity reactions occur and initiate appropriate medical treatment. (5.1)
- Hyperphosphatemia and Risk of Nephrocalcinosis: For patients already taking CRYSVITA, dose interruption and/or dose reduction may be required based on a patient's serum phosphorus levels. (5.2, 6.1)
- Hypercalcemia: Increases in serum calcium been reported. Monitor serum calcium and parathyroid hormone levels in patients at high risk for hypercalcemia before and during treatment. (5.3)
- Injection Site Reactions: Administration of CRYSVITA may result in local injection site reactions. Discontinue CRYSVITA if severe injection site reactions occur and administer appropriate medical treatment. (5.4, 6.1)

6 ADVERSE REACTIONS

- Most common adverse reactions (≥25% in the CRYSVITA group and > Active Control) in pediatric XLH patients are: pyrexia, injection site reaction, cough, vomiting, pain in extremity, headache, tooth abscess, dental caries. (6.1)
- Most common adverse reactions (>5% and in at least 2 patients more than placebo) in adult XLH patients are: back pain, headache, tooth infection, restless legs syndrome, vitamin D decreased, dizziness, constipation, muscle spasms, blood phosphorus increased. (6.1)
- Most common adverse reactions (>10%) in TIO patients are: tooth abscess, muscle spasms, dizziness, constipation, injection site reaction, rash, and headache. (6.1)

To report SUSPECTED ADVERSE REACTIONS, contact Kyowa Kirin, Inc. at 1-844-768-3544 or FDA at 1-800-FDA-1088 or www.fda.gov/medwatch.

FULL PRESCRIBING INFORMATION

1 INDICATIONS AND USAGE

1.1 X-linked Hypophosphatemia

CRYSVITA is indicated for the treatment of X-linked hypophosphatemia (XLH) in adult and pediatric patients 6 months of age and older.

1.2 Tumor-induced Osteomalacia

CRYSVITA is indicated for the treatment of FGF23-related hypophosphatemia in tumor-induced osteomalacia (TIO) associated with phosphaturic mesenchymal tumors that cannot be curatively resected or localized in adult and pediatric patients 2 years of age and older.

2 DOSAGE AND ADMINISTRATION

2.1 Important Information Prior to Initiation of CRYSVITA

Prior to starting CRYSVITA, discontinue oral phosphate and/or active vitamin D analogs (e.g. calcitriol, paricalcitol, doxercalciferol, calcifediol) for one week [see Contraindications (4), Warnings and Precautions (5.3)].

Prior to starting CRYSVITA, fasting serum phosphorus concentration should be below the reference range for age [see Contraindications (4)].

In patients at high risk for hypercalcemia (e.g., pre-existing hyperparathyroidism, prolonged immobilization, dehydration, hypervitaminosis D, or renal impairment) assess serum calcium and parathyroid hormone levels prior to starting CRYSVITA [see Warnings and Precautions (5.3)].

CRYSVITA is administered by subcutaneous injection and should be administered by a healthcare provider.

The maximum volume of CRYSVITA per injection is 1.5 mL. If multiple injections are required, administer at different injection sites.

2.2 Recommended Dosage for Pediatric Patients with X-linked Hypophosphatemia (6 months to less than 18 years of age)

For patients who weigh less than 10 kg, the recommended starting dosage is 1 mg/kg of body weight, rounded to the nearest 1 mg, administered every two weeks.

For patients who weigh 10 kg and greater, the recommended starting dose regimen is 0.8 mg/kg of body weight, rounded to the nearest 10 mg, administered every two weeks. The minimum starting dose is 10 mg up to a maximum dose of 90 mg.

After initiation of treatment with CRYSVITA, measure fasting serum phosphorus every 4 weeks for the first 3 months of treatment, and thereafter as appropriate. If serum phosphorus is above the lower limit of the reference range for age and below 5 mg/dL, continue treatment with the same dose. Follow dose adjustment schedule below to maintain serum phosphorus within the reference range for age.

Dose Adjustment

Reassess fasting serum phosphorus level 4 weeks after dose adjustment.

Do not adjust CRYSVITA more frequently than every 4 weeks.

Dose Increase:

For patients who weigh less than 10 kg, if serum phosphorus is below the reference range for age, the dose may be increased to 1.5 mg/kg, rounded to the nearest 1 mg, administered every two weeks. If additional dose increases are needed, the dose may be increased to the maximum dose of 2 mg/kg, rounded to the nearest 1 mg, administered every two weeks.

For patients who weigh 10 kg or greater, if serum phosphorus is below the reference range for age, the dose may be increased stepwise up to approximately 2 mg/kg, administered every two weeks (maximum dose of 90 mg) according to the dosing schedule shown in Table 1.

Table 1: XLH Pediatric Dose Schedule for Stepwise Dose Increase for Patients Weighing 10 kg or More
Body Weight (kg) | Starting Dose (mg) | First Dose Increase to (mg) | Second Dose Increase to (mg)
10 – 14 | 10 | 15 | 20
15 – 18 | 10 | 20 | 30
19 – 31 | 20 | 30 | 40
32 – 43 | 30 | 40 | 60
44 – 56 | 40 | 60 | 80
57 – 68 | 50 | 70 | 90
69 – 80 | 60 | 90 | 90
81 – 93 | 70 | 90 | 90
94 – 105 | 80 | 90 | 90
106 and greater | 90 | 90 | 90

Dose Decrease:

If serum phosphorus is above 5 mg/dL, withhold the next dose and reassess the serum phosphorus level in 4 weeks. The patient must have serum phosphorus below the reference range for age to reinitiate CRYSVITA. Once serum phosphorus is below the reference range for age, treatment may be restarted.

For patients who weigh less than 10 kg, restart CRYSVITA at 0.5 mg/kg of body weight, rounded to the nearest 1 mg, administered every two weeks. For patients who weigh 10 kg or more, restart CRYSVITA according to the dose schedule shown in Table 2.

Table 2: XLH Pediatric Dose Schedule for Re-Initiation of Therapy for Patients Weighing 10 kg or More
Previous Dose (mg) | Re-Initiation Dose (mg)
10 | 5
15 | 10
20 | 10
30 | 10
40 | 20
50 | 20
60 | 30
70 | 30
80 | 40
90 | 40

After a dose decrease, reassess serum phosphorus level 4 weeks after the dose adjustment. If the level remains below the reference range for age after the re-initiation dose, the dose can be adjusted as outlined under Dose Increase.

2.3 Recommended Dosage for Adult Patients with X-linked Hypophosphatemia (18 years of age and older)

The recommended dosage regimen in adults is 1 mg/kg body weight, rounded to the nearest 10 mg up to a maximum dose of 90 mg, administered every four weeks.

After initiation of treatment with CRYSVITA, assess fasting serum phosphorus on a monthly basis, measured 2 weeks post-dose, for the first 3 months of treatment, and thereafter as appropriate. If serum phosphorus is within the normal range, continue with the same dose.

Dose Decrease

Reassess fasting serum phosphorus level 2 weeks after dose adjustment.

Do not adjust CRYSVITA more frequently than every 4 weeks.

If serum phosphorus is above the normal range, withhold the next dose and reassess the serum phosphorus level after 4 weeks. The patient must have serum phosphorus below the normal range to be able to reinitiate CRYSVITA. Once serum phosphorus is below the normal range, treatment may be restarted at approximately half the initial starting dose up to a maximum dose of 40 mg every 4 weeks according to the dose schedule shown in Table 3. Reassess serum phosphorus 2 weeks after any change in dose.

Table 3: XLH Adult Dose Schedule for Re-Initiation of Therapy
Previous Dose (mg) | Re-Initiation Dose (mg)
40 | 20
50 | 20
60 | 30
70 | 30
80 and greater | 40

2.4 Recommended Dosage for Pediatric Patients with Tumor-induced Osteomalacia (2 years to less than 18 years of age)

The recommended starting dosage for pediatrics is 0.4 mg/kg body weight administered every 2 weeks, rounded to the nearest 10 mg, up to a maximum dose of 2 mg/kg not to exceed 180 mg, administered every 2 weeks.

After initiation of treatment with CRYSVITA, assess fasting serum phosphorus on a monthly basis, measured 2 weeks post-dose, for the first 3 months of treatment, and thereafter as appropriate. If serum phosphorus is within the reference range for age, continue with the same dose. Follow the dose adjustment schedule below to maintain serum phosphorus within the reference range for age.

Dose Adjustment

Reassess fasting serum phosphorus level 4 weeks after dose adjustment.

Do not adjust CRYSVITA more frequently than every 4 weeks.

Dose Increase

If serum phosphorus is below the reference range for age, the dose should be titrated in accordance with Table 4 up to the maximum dose of 2 mg/kg every 2 weeks. The maximum dose should not exceed 180 mg.

Table 4: TIO Pediatric Dose Schedule for Stepwise Dose Increase for Patients Weighing 10 kg or more
Body Weight (kg) | Starting Dose (mg) | First Dose Increase to (mg) | Second Dose Increase to (mg) | Third Dose [The table shows a dose increase up to 1.5 mg/kg. Further dose increases to a maximum of 2 mg/kg not to exceed 180 mg, administered every 2 weeks should be calculated by the physician.] Increase to (mg)
10 – 14 | 5 | 10 | 15 | 20
15 – 18 | 5 | 10 | 20 | 25
19 – 31 | 10 | 20 | 25 | 30
32 – 43 | 10 | 30 | 40 | 50
44 – 56 | 20 | 40 | 50 | 70
57 – 68 | 20 | 50 | 70 | 90
69 – 80 | 30 | 60 | 80 | 100
81 – 93 | 30 | 70 | 100 | 120
94 – 105 | 40 | 80 | 110 | 140
106 and greater | 40 | 90 | 130 | 160

Dose Decrease

If serum phosphorus is above the reference range for age, withhold the next dose and reassess the serum phosphorus level in 4 weeks. The patient must have serum phosphorus below the reference range for age to reinitiate CRYSVITA. Once serum phosphorus is below the reference range for age, treatment may be restarted at approximately half the initial starting dose, up to a maximum dose of 180 mg administered every 2 weeks for pediatrics. After a dose decrease, reassess serum phosphorus level 4 weeks after the dose adjustment. If the level remains below the reference range for age after the re-initiation dose, the dose can be adjusted as outlined per Table 4.

Dose Interruption

If a patient undergoes treatment of the underlying tumor (i.e., surgical excision or radiation therapy) CRYSVITA treatment should be interrupted and serum phosphorus reassessed after treatment has been completed. CRYSVITA dose should be restarted at the patient's initiation dose if serum phosphorus remains below the lower limit of normal. Follow dose adjustment per Table 4 to maintain serum phosphorus within the reference range for age.

2.5 Recommended Dosage for Adult Patients with Tumor-induced Osteomalacia (18 years of age and older)

The recommended starting dosage for adults is 0.5 mg/kg body weight administered every 4 weeks, rounded to the nearest 10 mg, up to a maximum dose of 2 mg/kg not to exceed 180 mg, administered every 2 weeks.

After initiation of treatment with CRYSVITA, assess fasting serum phosphorus on a monthly basis, measured 2 weeks post-dose, for the first 3 months of treatment, and thereafter as appropriate. If serum phosphorus is within the normal range, continue with the same dose. Follow the dose adjustment schedule below to maintain serum phosphorus within the reference range.

Dose Adjustment

Reassess fasting serum phosphorus level 2 weeks after dose adjustment.

Do not adjust CRYSVITA more frequently than every 4 weeks.

Dose Increase

If serum phosphorus is below the normal range, the dose should be titrated in accordance with Table 5 up to the maximum dose of 2 mg/kg not to exceed 180 mg, administered every 2 weeks. For those individuals not reaching a serum phosphorus greater than the lower limit of the normal range, physicians may consider dividing total dose administered every 4 weeks and administering every 2 weeks.

Table 5: TIO Dose Schedule [Rounded to the nearest 10 mg.] for Stepwise [Do not adjust CRYSVITA more frequently than every 4 weeks.] Dose Increase for Adults (18 years of age and older)
 | Starting Dose | First Dose Increase [For those individuals not reaching a serum phosphorus greater than the lower limit of the normal range, physicians may consider dividing total dose administered every 4 weeks and administering every 2 weeks.] | Second Dose Increase | Third Dose Increase | Fourth Dose Increase | Fifth Dose Increase (maximum dose)
If serum phosphorus 2 weeks post-dose adjustment is below lower limit of normal | 0.5 mg/kg every 4 weeks | Increase to: 1 mg/kg every 4 weeks OR 0.5 mg/kg every 2 weeks | Increase to: 1.5 mg/kg every 4 weeks [In patients with high body weight, if the calculated dose is greater than 180 mg every 4 weeks, move to a divided dose every 2 weeks.] OR 0.75 mg/kg every 2 weeks | Increase to: 2 mg/kg every 4 weeks OR 1 mg/kg every 2 weeks | Increase to: 1.5 mg/kg not to exceed 180 mg every 2 weeks | Increase to: 2 mg/kg not to exceed 180 mg every 2 weeks

Dose Decrease

If serum phosphorus is above the normal range, withhold the next dose and reassess the serum phosphorus level in 4 weeks. The patient must have serum phosphorus below the reference range to reinitiate CRYSVITA. Once serum phosphorus is below the reference range, treatment may be restarted at approximately half the initial starting dose, up to a maximum dose of 180 mg administered every 2 weeks for adults. After a dose decrease, reassess serum phosphorus level 2 weeks after the dose adjustment. If the level remains below the reference range after the re-initiation dose, the dose can be adjusted as outlined per Table 5.

Dose Interruption

If a patient undergoes treatment of the underlying tumor (i.e., surgical excision or radiation therapy) CRYSVITA treatment should be interrupted and serum phosphorus reassessed after treatment has been completed. CRYSVITA dose should be restarted at the patient’s initiation dose if serum phosphorus remains below the lower limit of normal. Follow dose adjustment per Table 5 to maintain serum phosphorus within the reference range.

2.6 Missed Dose

If a patient misses a dose, resume CRYSVITA as soon as possible at the prescribed dose. To avoid missed doses, treatments may be administered 3 days either side of the scheduled treatment date.

2.7 25-Hydroxy Vitamin D Supplementation

Monitor 25-hydroxy vitamin D levels. Supplement with cholecalciferol or ergocalciferol to maintain 25-hydroxy vitamin D levels in the normal range for age. Do not administer active Vitamin D analogs during CRYSVITA treatment [see Contraindications (4)].

2.8 General Considerations for Subcutaneous Administration

Injection sites should be rotated with each injection administered at a different anatomic location (upper arms, upper thighs, buttocks, or any quadrant of abdomen) than the previous injection. Do not inject into moles, scars, or areas where the skin is tender, bruised, red, hard, or not intact. If a given dose on a dosing day requires multiple vials of CRYSVITA, contents from two vials can be combined for injection. The maximum volume of CRYSVITA per injection is 1.5 mL. If multiple injections are required on a given dosing day, administer at different injection sites. Monitor for signs of reactions [see Warnings and Precautions (5.4)].

Visually inspect CRYSVITA for particulate matter and discoloration prior to administration. CRYSVITA is a sterile, preservative-free, clear to slightly opalescent and colorless to pale brown-yellow solution for subcutaneous injection. Do not use if the solution is discolored or cloudy or if the solution contains any particles or foreign particulate matter.

3 DOSAGE FORMS AND STRENGTHS

Injection: 10 mg/mL, 20 mg/mL, or 30 mg/mL clear to slightly opalescent and colorless to pale brown-yellow solution in a single-dose vial.

4 CONTRAINDICATIONS

CRYSVITA is contraindicated:

- In concomitant use with oral phosphate and/or active vitamin D analogs (e.g. calcitriol, paricalcitol, doxercalciferol, calcifediol) due to the risk of hyperphosphatemia [see Warnings and Precautions (5.2) and Drug Interactions (7.1)].
- When serum phosphorus is within or above the normal range for age [see Warnings and Precautions (5.2)].
- In patients with severe renal impairment or end stage renal disease because these conditions are associated with abnormal mineral metabolism [see Use In Specific Population (8.6)].

5 WARNINGS AND PRECAUTIONS

5.1 Hypersensitivity

Hypersensitivity reactions (e.g. rash, urticaria) have been reported in patients with CRYSVITA. Discontinue CRYSVITA if serious hypersensitivity reactions occur and initiate appropriate medical treatment [see Adverse Reactions (6.1)].

5.2 Hyperphosphatemia and Risk of Nephrocalcinosis

Increases in serum phosphorus to above the upper limit of normal may be associated with an increased risk of nephrocalcinosis. For patients already taking CRYSVITA, dose interruption and/or dose reduction may be required based on a patient's serum phosphorus levels. Patients with tumor-induced osteomalacia who undergo treatment of the underlying tumor should have dosing interrupted and adjusted to prevent hyperphosphatemia [see Dosage and Administration (2) and Adverse Reactions (6.1)].

5.3 Hypercalcemia

Increases in serum calcium have been reported in patients treated with CRYSVITA. Patients with risk factors such as, pre-existing hyperparathyroidism, prolonged immobilization, dehydration, hypervitaminosis D, or renal impairment, are at higher risk of hypercalcemia. Monitor these patients for serum calcium and parathyroid hormone levels before and during CRYSVITA treatment for moderate to severe hypercalcemia. In patients with moderate to severe hypercalcemia, CRYSVITA should not be administered until hypercalcemia is adequately managed.

5.4 Injection Site Reactions

Administration of CRYSVITA may result in local injection site reactions. Discontinue CRYSVITA if severe injection site reactions occur and administer appropriate medical treatment [see Adverse Reactions (6.1)].

6 ADVERSE REACTIONS

The following adverse reactions are described below and elsewhere in the labeling:

- Hypersensitivity [see Warnings and Precautions (5.1)]
- Hyperphosphatemia and Risk of Nephrocalcinosis [see Warnings and Precautions (5.2)]
- Hypercalcemia [see Warnings and Precautions (5.3)
- Injection Site Reactions [see Warnings and Precautions (5.4)]

6.1 Clinical Trials Experience

Because clinical trials are conducted under widely varying conditions, adverse reaction rates observed in the clinical trials of a drug cannot be directly compared to rates in the clinical trials of another drug and may not reflect the rates observed in practice.

Adverse Reactions in Pediatric Patients with XLH

CRYSVITA was studied in three pediatric XLH studies. Study 1 is a randomized, open-label phase 3 study in XLH patients ages 1 to 12 years, who were randomized to treatment with CRYSVITA or treatment with active control of oral phosphate and active vitamin D (CRYSVITA N = 29, Active Control N = 32). Study 2 is an open-label phase 2 study in XLH patients ages 5 to 12 years (N = 52). Study 3 is an open-label phase 2 study in XLH patients ages 1 to less than 5 years (N = 13). Overall, the patient population was 1-12 years (mean age 7.0 years), 49% male, and 88% white.

In Study 1, patients randomized to CRYSVITA received a mean dose of approximately 0.90 mg/kg (range 0.8-1.2 mg/kg) every 2 weeks. All patients in this group and the active control group completed 64 weeks of treatment.

Adverse reactions occurring in ≥ 10% of subjects in the CRYSVITA group, with higher frequency than in the subjects in the active control group, through the 64-week treatment period in Study 1 are shown in Table 6.

Table 6: Adverse Reactions Reported in 10% or More of CRYSVITA-Treated Pediatric Patients and with Higher Frequency Than the Active Control Group in Study 1
Adverse Reaction | CRYSVITA (N=29) n (%) | Active Control (N=32) n (%)
Pyrexia | 16 (55) | 6 (19)
Injection site reaction [Injection site reaction includes: injection site reaction, injection site erythema, injection site pruritus, injection site swelling, injection site pain, injection site rash, injection site bruising, injection site discoloration, injection site discomfort, injection site hematoma, injection site hemorrhage, injection site induration, injection site macule, and injection site urticaria] | 15 (52) | 0 (0)
Cough [Cough includes: cough and productive cough] | 15 (52) | 6 (19)
Vomiting | 12 (41) | 8 (25)
Pain in extremity | 11 (38) | 10 (31)
Headache | 10 (34) | 6 (19)
Tooth abscess [Tooth abscess includes: tooth abscess, tooth infection, toothache] | 10 (34) | 4 (13)
Dental caries | 9 (31) | 2 (6)
Diarrhea | 7 (24) | 2 (6)
Vitamin D decreased [Vitamin D decreased includes: vitamin D deficiency, blood 25-hydroxycholecalciferol decreased, and vitamin D decreased] | 7 (24) | 1 (3)
Constipation | 5 (17) | 0 (0)
Rash [Rash includes: rash, rash pruritic, rash maculopapular, rash erythematous, rash generalized and rash pustular] | 4 (14) | 2 (6)
Nausea | 3 (10) | 1 (3)
n = number of patients with an event; N = total number of patients who received at least one dose of CRYSVITA or active control

In Study 2, 26 of the patients received CRYSVITA at a mean dose of 1.05 mg/kg (range 0.4 – 2.0 mg/kg) every 2 weeks at Week 64; the other 26 patients received CRYSVITA every 4 weeks. The mean duration of exposure in Study 2 was 124 weeks. In Study 3, patients received CRYSVITA at a mean dose of 0.90 mg/kg (range 0.8-1.2 mg/kg) every 2 weeks at Week 40. The mean duration of exposure in Study 3 was 45 weeks.

Adverse reactions occurring in more than 10% of CRYSVITA-treated patients from Studies 2 and 3 are shown in Table 7.

Table 7: Adverse Reactions Reported in More Than 10% of Pediatric Patients Receiving CRYSVITA in Studies 2 and 3
Adverse Reaction | Study 2 (N=52) n (%) | Study 3 (N=13) n (%) | Overall (N=65) n (%)
Headache | 38 (73) | 1 (8) | 39 (60)
Injection site reaction [Injection site reaction includes: injection site reaction, injection site erythema, injection site pruritus, injection site swelling, injection site pain, injection site rash, injection site bruising, injection site discoloration, injection site discomfort, injection site hematoma, injection site hemorrhage, injection site induration, injection site macule, and injection site urticaria] | 35 (67) | 3 (23) | 38 (59)
Vomiting | 25 (48) | 6 (46) | 31 (48)
Pyrexia | 23 (44) | 8 (62) | 31 (48)
Pain in extremity | 24 (46) | 3 (23) | 27 (42)
Vitamin D decreased [Vitamin D decreased includes: vitamin D deficiency, blood 25-hydroxycholecalciferol decreased, and vitamin D decreased] | 19 (37) | 2 (15) | 21 (32)
Rash [Rash includes: rash, rash pruritic, rash maculopapular, and rash pustular] | 14 (27) | 1 (8) | 15 (23)
Toothache | 12 (23) | 2 (15) | 14 (22)
Myalgia | 9 (17) | 1 (8) | 10 (15)
Tooth abscess | 8 (15) | 3 (23) | 11 (17)
Dizziness [Dizziness includes: dizziness, and dizziness exertional] | 8 (15) | 0 (0) | 8 (12)
n = number of patients with an event; N = total number of patients who received at least one dose of CRYSVITA

Hypersensitivity Reactions

In Study 1 (N=29 for CRYSVITA arm), the most frequent hypersensitivity reactions were rash (10%), injection site rash (10%) and injection site urticaria (7%). In Studies 2 and 3 (N=65), the most frequent hypersensitivity reactions were rash (22%), injection site rash (6%), and urticaria (5%).

Hyperphosphatemia

In pediatric studies, no events of hyperphosphatemia were reported.

Injection Site Reactions (ISR)

In Study 1 (N=29 for CRYSVITA arm), 52% of the patients had a local injection site reaction (e.g. injection site urticaria, erythema, rash, swelling, bruising, pain, pruritus, and hematoma) at the site of CRYSVITA injection. In Studies 2 and 3 (N=65), approximately 58% of the patients had a local injection site reaction at the site of CRYSVITA injection. Injection site reactions were generally mild in severity, occurred within 1 day of injection, lasted approximately 1 to 3 days, required no treatment, and resolved in almost all instances.

Adverse Reactions in Adult Patients with XLH

The safety of CRYSVITA in adult patients with XLH was demonstrated in a randomized, double-blind, placebo-controlled study (Study 4) of 134 patients, age 20-63 years (mean age 41 years), of whom most were white/Caucasian (81%) and female (65%). A total of 68 and 66 patients received at least one dose of CRYSVITA or placebo, respectively. The mean dose of CRYSVITA was 0.95 mg/kg (range 0.3 – 1.2 mg/kg) subcutaneously every 4 weeks. Adverse reactions reported in more than 5% of CRYSVITA-treated patients and 2 patients or more than with placebo from the 24-week placebo-controlled portion of Study 4 are shown in Table 8.

Table 8: Adverse Reactions Occurring in More Than 5% of CRYSVITA-Treated Adult Patients and in at Least 2 Patients More Than with Placebo in the 24-Week Placebo-Controlled Period of Study 4
Adverse Reaction | CRYSVITA (N=68) n (%) | Placebo (N=66) n (%)
Back pain | 10 (15) | 6 (9)
Headache [Headache includes: headache, and head discomfort] | 9 (13) | 6 (9)
Tooth infection [Tooth infection includes: tooth abscess, and tooth infection] | 9 (13) | 6 (9)
Restless legs syndrome | 8 (12) | 5 (8)
Vitamin D decreased [Vitamin D decreased includes: vitamin D deficiency, blood 25-hydroxycholecalciferol decreased, and vitamin D decreased] | 8 (12) | 3 (5)
Dizziness | 7 (10) | 4 (6)
Muscle spasms | 5 (7) | 2 (3)
Constipation | 6 (9) | 0 (0)
Blood phosphorus increased [Blood phosphorus increased includes: blood phosphorus increased, and hyperphosphatemia] | 4 (6) | 0 (0)
n = number of patients with an event; N = total number of patients who received at least one dose of CRYSVITA or placebo

The 24-week placebo controlled study was followed by a 24-week open-label treatment period in which all patients received CRYSVITA subcutaneously every 4 weeks. No new adverse reactions were identified in the open-label extension period.

Hypersensitivity Reactions

In the double-blind period of Study 4, approximately 6% of patients in both the CRYSVITA and placebo treatment groups experienced a hypersensitivity event. The events were mild or moderate and did not require discontinuation.

Hyperphosphatemia

In the double-blind period of Study 4, 7% of patients in the CRYSVITA treatment group experienced hyperphosphatemia meeting the protocol-specified criteria for dose reduction (either a single serum phosphorus greater than 5.0 mg/dL or serum phosphorus greater than 4.5 mg/dL [the upper limit of normal] on two occasions). The hyperphosphatemia was managed with dose reduction. The dose for all patients meeting the protocol-specified criteria was reduced 50 percent. A single patient required a second dose reduction for continued hyperphosphatemia.

Injection Site Reactions (ISR)

In the double-blind period of Study 4, approximately 12% of patients in both the CRYSVITA and placebo treatment groups had a local reaction (e.g. injection site reaction, erythema, rash, bruising, pain, pruritus, and hematoma) at the site of the injection. Injection site reactions were generally mild in severity, occurred within 1 day of injection, lasted approximately 1 to 3 days, required no treatment, and resolved in almost all instances.

Restless Legs Syndrome (RLS)

In the double-blind period of Study 4, approximately 12% of the CRYSVITA treatment group had worsening of baseline restless legs syndrome (RLS) or new onset RLS of mild to moderate severity; these events did not lead to dose discontinuation. Nonserious RLS has also been reported in other repeat dose adult XLH studies; in one case, worsening baseline RLS led to drug discontinuation and subsequent resolution of the event.

Spinal Stenosis

Spinal stenosis is prevalent in adults with XLH and spinal cord compression has been reported. In the CRYSVITA phase 2 and phase 3 studies of adults with XLH (total N=176), a total of 7 patients underwent spinal surgery. Most of these cases appeared to involve progression of a pre-existing spinal stenosis. It is unknown if CRYSVITA therapy exacerbates spinal stenosis or spinal cord compression.

Adverse Reactions in Patients with TIO

The safety of CRYSVITA in patients with TIO was demonstrated in two single-arm clinical studies (Study 6 and Study 7) that enrolled a total of 27 patients. Fourteen patients were male, and patients ranged from 33 to 73 years of age. The mean dose of CRYSVITA was 0.77 mg/kg every 4 weeks and the mean duration of exposure was 121 weeks.

Adverse reactions reported in adult TIO patients in the pooled data from Study 6 and Study 7 are shown in Table 9.

Table 9: Adverse Reactions Reported in Adult Patients with TIO Based on Study 6 and Study 7 (N=27)
Adverse Reaction | Overall (N=27) n (%)
Tooth abscess [Tooth abscess is defined by PTs "Tooth abscess" and "Tooth ache"] | 5 (19)
Muscle spasms | 5 (19)
Dizziness | 4 (15)
Constipation | 4 (15)
Injection site reaction [Injection Site Reactions is defined by PTs "Injection Site Reaction", "Injection Site Pain" and "Injection Site Swelling"] | 4 (15)
Rash [Rash is defined by PTs "Rash" and "Rash papular"] | 4 (15)
Headache | 3 (11)
Vitamin D deficiency | 2 (7)
Hyperphosphatemia | 2 (7)
Restless legs syndrome | 2 (7)

Hypersensitivity reactions

In the pooled data for Studies 6 and 7, 22% of patients experienced a hypersensitivity reaction. The most frequent hypersensitivity reactions were eczema (11%) and rash (11%). The events were mild or moderate in severity.

Hyperphosphatemia

In the pooled data for Studies 6 and 7, 2 patients (7%) experienced hyperphosphatemia which was managed with dose reduction.

Injection site reactions

The frequency of injection site reactions was 15% (injection site reaction, injection site pain, and injection site swelling). The injection site reactions were generally mild in severity, required no treatment and resolved in all cases.

Restless Legs Syndrome

In the pooled data for Studies 6 and 7, 2 patients (7%) experienced symptoms of restless legs syndrome, which were mild and did not require treatment interruption.

6.2 Postmarketing Experience

The following adverse reactions have been identified during postapproval use of CRYSVITA. Because these reactions are reported voluntarily from a population of uncertain size, it is not always possible to reliably estimate their frequency or establish a causal relationship to drug exposure.

Metabolism and nutrition disorders: Hypercalcemia

Skin and subcutaneous tissue disorders: Urticaria

Investigations: Blood phosphorus increased in pediatric XLH patients, blood parathyroid hormone increased

7 DRUG INTERACTIONS

7.1 Oral Phosphate and Active Vitamin D Analogs

Concomitant use of CRYSVITA with oral phosphate and/or active vitamin D analogs will increase phosphate concentrations greater than expected with CRYSVITA alone. This increase may result in hyperphosphatemia which can induce nephrocalcinosis.

Concomitant use of CRYSVITA with oral phosphate and/or active vitamin D analogs is contraindicated.

8 USE IN SPECIFIC POPULATIONS

8.1 Pregnancy

Risk Summary

There are no available data on CRYSVITA use in pregnant women to inform a drug-associated risk of adverse developmental outcomes. In utero, burosumab-twza exposure in cynomolgus monkeys did not result in teratogenic effects. Adverse effects such as late fetal loss and preterm birth were observed in pregnant cynomolgus monkeys, however, these effects are unlikely to indicate clinical risk because they occurred at a drug exposure that was 15-fold higher, by AUC, than the human exposure at the maximum recommended human dose (MRHD) of 2 mg/kg every 2 weeks and were accompanied by maternal hyperphosphatemia and placental mineralization (see Data). Serum phosphorus levels should be monitored throughout pregnancy [see Dosage and Administration (2.2)]. Report pregnancies to the Kyowa Kirin, Inc. Adverse Event reporting line at 1-844-768-3544.

The background risk of major birth defects and miscarriage for the indicated population is unknown; however, the estimated background risk in the U.S. general population of major birth defects is 2% to 4% and of miscarriage is 15% to 20% of clinically recognized pregnancies.

Data

Animal Data

In a reproductive toxicity study in pregnant cynomolgus monkeys, burosumab-twza was administered intravenously once every two weeks from Day 20 of pregnancy to parturition or cesarean section on Day 133, which includes the period of organogenesis, at doses of 0.2-, 2- and 15-fold human exposure at the adult MRHD of 2 mg/kg every 2 weeks. The treatment did not result in teratogenic effects in fetuses or offspring. An increase in late fetal loss, a shortened gestation period, and an increased incidence of preterm births were observed at 15-fold human exposure at the adult MRHD of 2 mg/kg every 2 weeks, concomitant with maternal hyperphosphatemia and placental mineralization. Burosumab-twza was detected in serum from fetuses indicating transport across the placenta. Hyperphosphatemia but no ectopic mineralization was present in fetuses and offspring of dams exposed to 15-fold human exposure at the MRHD of 2 mg/kg dose every 2 weeks. Burosumab-twza did not affect pre- and postnatal growth including survivability of the offspring.

8.2 Lactation

Risk Summary

There is no information regarding the presence of burosumab-twza in human milk, or the effects of burosumab-twza on milk production or the breastfed infant. Maternal IgG is present in breast milk. However, the effects of local gastrointestinal exposure and limited systemic exposure to burosumab-twza in the breastfed infant are unknown. The lack of clinical data during lactation precludes a clear determination of the risk of CRYSVITA to an infant during lactation. Therefore, the developmental and health benefits of breastfeeding should be considered along with the mother's clinical need for CRYSVITA and any potential adverse effects on the breastfed infant from CRYSVITA or from the underlying maternal condition.

8.4 Pediatric Use

Safety and effectiveness of CRYSVITA have been established in pediatric patients 6 months and older. Safety and effectiveness in pediatric patients 1 year and older with XLH are based on one phase 3, open-label, active control study [61 patients 1-12 years of age (Study 1)] and two open-label studies [52 patients 5 to 12 years of age (Study 2), and 13 patients 1 to 4 years of age (Study 3)] evaluating serum phosphorus and radiographic findings. Safety and effectiveness in patients 6 months to 1 year and adolescents are supported by evidence from the studies in pediatric patients 1 year to less than 13 years of age with additional modeling and simulation of adult and pediatric pharmacokinetic (PK) and pharmacodynamic (PD) data to inform dosing [see Adverse Reactions (6.1) and Clinical Studies (14)].

Safety and effectiveness for CRYSVITA in pediatric patients with XLH below the age of 6 months have not been established.

Safety and effectiveness of CRYSVITA in pediatric patients 2 years and older with TIO are supported by evidence from the studies in adult patients with TIO with additional modeling and simulation of PK data from adult and pediatric XLH patients and adult TIO patients to inform dosing.

Safety and effectiveness for CRYSVITA in pediatric patients with TIO below the age of 2 years have not been established.

8.5 Geriatric Use

Clinical studies of CRYSVITA did not include sufficient numbers of patients aged 65 and over to determine whether they respond differently from younger patients. Other reported clinical experience has not identified differences in responses between the elderly and younger patients. In general, dose selection for an elderly patient should be cautious, usually starting at the low end of the dosing range, reflecting the greater frequency of decreased hepatic, renal, or cardiac function, and of concomitant disease or other drug therapy.

8.6 Renal Impairment

The effect of renal impairment on the pharmacokinetics of burosumab-twza is unknown. However, renal impairment can induce abnormal mineral metabolism which will increase phosphate concentrations greater than expected with CRYSVITA alone. This increase may result in hyperphosphatemia which can induce nephrocalcinosis.

CRYSVITA is contraindicated in patients with severe renal impairment, defined as:

- pediatric patients with estimated glomerular filtration rate (eGFR) 15 mL/min/1.73m^2 to 29 mL/min/1.73m^2 or end stage renal disease (eGFR < 15 mL/min/1.73m^2)
- adult patients with creatinine clearance (CLcr) 15 mL/min to 29 mL/min or end stage renal disease (CLcr < 15 mL/min).

10 OVERDOSAGE

There have been no reports of overdose with CRYSVITA. CRYSVITA has been administered in pediatric clinical trials without dose limiting toxicity using doses up to 2 mg/kg body weight with a maximal dose of 90 mg, administered every two weeks. In XLH adult clinical trials, no dose limiting toxicity has been observed using doses up to 1 mg/kg or a maximal total dose of 128 mg every 4 weeks. In non-XLH rabbits and cynomolgus monkeys, ectopic mineralization in multiple tissues and organs was observed at doses of burosumab-twza that resulted in supra-physiologic serum phosphate levels. Adverse effects on bone including reductions in bone mineral density, bone mineralization and bone strength were also observed at exposure greater than human exposure [see Nonclinical Toxicology (13.2)].

In case of overdose, it is recommended that serum phosphorus levels, serum calcium levels and renal function be measured immediately and monitored periodically until resolution to normal/baseline levels. In case of hyperphosphatemia, withhold CRYSVITA and initiate appropriate medical treatment.

11 DESCRIPTION

Burosumab-twza is a human immunoglobulin G subclass 1 (IgG1), anti-human fibroblast growth factor 23 (FGF23) antibody produced by recombinant DNA technology using Chinese hamster ovary cells. Burosumab-twza is composed of two heavy chain (γ1-chain) molecules and two light chain (κ-chain) molecules. Each heavy chain has an N-linked carbohydrate moiety at asparagine 297 (Asn297). The molecular weight of burosumab-twza determined by mass spectrometry is approximately 147,000.

CRYSVITA (burosumab-twza) injection for subcutaneous administration is supplied as a sterile, preservative-free, clear to slightly opalescent and colorless to pale brown-yellow solution in a single-dose vial.

Each 1 mL of solution contains 10 mg, 20 mg or 30 mg of burosumab-twza, L-histidine (1.55 mg), L-methionine (1.49 mg), polysorbate 80 (0.5 mg), D-sorbitol (45.91 mg) in Water for Injection, USP. Hydrochloric acid may be used to adjust to a pH of 6.25.

12 CLINICAL PHARMACOLOGY

12.1 Mechanism of Action

X-linked hypophosphatemia is caused by excess fibroblast growth factor 23 (FGF23) which suppresses renal tubular phosphate reabsorption and the renal production of 1,25 dihydroxy vitamin D. Burosumab-twza binds to and inhibits the biological activity of FGF23 restoring renal phosphate reabsorption and increasing the serum concentration of 1,25 dihydroxy vitamin D.

12.2 Pharmacodynamics

Following SC administration in XLH and TIO patients, higher burosumab-twza concentrations were associated with greater increase of serum phosphorus levels. The increase in serum phosphorus was reversible and returned to baseline with elimination of systemic burosumab-twza.

Ratio of renal tubular maximum reabsorption rate of phosphate to glomerular filtration rate (TmP/GFR) showed dose-dependent increases from baseline [see Clinical Studies (14)].

Elevation in serum total FGF23 was observed after initiation of burosumab-twza treatment, however, the clinical implication is unknown.

12.3 Pharmacokinetics

The following pharmacokinetic parameters were observed in patients with XLH administered the approved recommended starting dosage based on a 70 kg patient, unless otherwise specified. Based on the population PK analysis, the PK characteristics of burosumab-twza were similar between patients with XLH and TIO.

Burosumab-twza exhibited linear pharmacokinetics following SC injections within the dose range of 0.1 to 1 mg/kg (0.08 to 0.8 times the maximum approved recommended dosage based on a 70 kg patient with XLH).

The steady-state trough mean (± SD) concentration of burosumab-twza was 5.8 (± 3.4) mcg/mL in adult XLH patients.

Absorption

The burosumab-twza mean Tmax values ranged from 8 to 11 days.

Distribution

The apparent volume of distribution of burosumab-twza is 8 L.

Elimination

The apparent clearance is 0.290 L/day. The half-life of burosumab-twza is approximately 19 days.

Metabolism

The exact pathway for burosumab-twza metabolism has not been characterized. Burosumab-twza is expected to be degraded into small peptides and amino acids via catabolic pathways.

Specific Populations

No clinical significant difference in burosumab-twza pharmacokinetics was observed based on age.

The effect of renal or hepatic impairment on the pharmacokinetics of burosumab-twza is unknown.

Pediatric Patients

The steady-state trough concentration was 15.8 (± 9.4) mcg/mL in XLH patients aged 5-12 years, and 11.2 (± 4.6) mcg/mL in XLH patients aged 1-4 years.

Body Weight

Clearance and volume of distribution of burosumab-twza increases with body weight.

Drug Interaction Studies

No drug interaction studies have been conducted with CRYSVITA.

12.6 Immunogenicity

As with all therapeutic proteins, there is potential for immunogenicity. The detection of antibody formation is highly dependent on the sensitivity and specificity of the assay. Additionally, the observed incidence of antibody (including neutralizing antibody) positivity in an assay may be influenced by several factors including assay methodology, sample handling, timing of sample collection, concomitant medications, and underlying disease. For these reasons, comparison of the incidence of antibodies to CRYSVITA in the studies described below with the incidence of antibodies in other studies or to other products may be misleading.

In XLH clinical studies, none (0/13) of the 1- to 4-year-old patients, 19% (10/52) of the 5- to 12-year- old patients, and 15% (20/131) of the adult patients tested positive for anti-drug antibodies (ADA) after receiving CRYSVITA. Among these, three 5- to 12-year-old patients tested positive for neutralizing antibodies. The presence of ADA was not associated with clinically relevant changes in pharmacokinetics, pharmacodynamics, efficacy, and safety of CRYSVITA in patients with XLH.

In one TIO clinical study, 14% (2/14) of the adult patients tested positive for ADA after receiving CRYSVITA. None of the ADA positive patients tested positive for neutralizing antibodies. In another TIO clinical study, none of the 13 adult patients tested positive for ADA after receiving CRYSVITA.

13 NONCLINICAL TOXICOLOGY

13.1 Carcinogenesis, Mutagenesis, Impairment of Fertility

The carcinogenic potential of burosumab-twza has not been evaluated in long term animal studies.

Studies have not been performed to evaluate the mutagenic potential of burosumab-twza.

No specific fertility studies have been performed in animals to evaluate the effects of burosumab-twza.

Toxicology studies with burosumab-twza of up to 40 weeks duration in cynomolgus monkeys did not show significant adverse effects on female reproductive organs at doses up to 16-fold human exposure at the maximum recommended human dose (MRHD) of 2 mg/kg every 2 weeks. In male monkeys, minimal mineralization of the rete testis or seminiferous tubules associated with hyperphosphatemia was observed at 3- to 9-fold human exposure at the MRHD of 2 mg/kg every 2 weeks, but semen analysis did not show any adverse effects.

13.2 Animal Toxicology and/or Pharmacology

In rabbits and cynomolgus monkeys, inhibition of FGF23 signaling by burosumab-twza increased serum phosphate and 1,25 dihydroxy vitamin D. Ectopic mineralization in multiple tissues and organs was observed at doses of burosumab-twza that resulted in supra-physiologic serum phosphate levels. In a study in wild type (WT) and hypophosphatemic Hyp mice, a murine model of XLH, ectopic mineralization was markedly less in Hyp mice.

In adult cynomolgus monkeys, burosumab-twza increased bone turnover, mineral content and/or mineral density and cortical thickness at 9- to 16-fold human exposure at the MRHD of 2 mg/kg every 2 weeks. Adverse effects on bone, including reductions in bone mineral density, bone mineralization and bone strength were observed in adult male monkeys at 9- to 11-fold human exposure at the MRHD of 2 mg/kg every 2 weeks.

In juvenile cynomolgus monkeys, burosumab-twza increased bone turnover, mineral content and/or mineral density and/or cortical thickness at 0.2- to 2-fold clinical pediatric exposure. Bone mineralization was decreased in a male monkey at 2-fold pediatric exposure but there was no effect on bone strength. Burosumab-twza did not affect bone development in juvenile monkeys at doses up to 2-fold pediatric exposure.

14 CLINICAL STUDIES

14.1 Pediatric X-linked Hypophosphatemia

CRYSVITA has been evaluated in three studies enrolling a total of 126 pediatric patients with XLH.

Study 1 (NCT 02915705) is a 64-week randomized, open-label study in 61 pediatric XLH patients, 1 to 12 years old that compared treatment with CRYSVITA to active control (oral phosphate and active vitamin D). At time of first dose the mean age of patients was 6.3 years and 44% were male. All patients had radiographic evidence of rickets at baseline, with an RSS score of ≥ 2.0 and had received oral phosphate and active vitamin D analogs for a mean (SD) duration of 4 (3.1) years. Oral phosphate and active vitamin D analogs were discontinued prior to study enrollment for a 7-day washout period and then reinitiated for patients in the active control group. Patients were randomized to receive either CRYSVITA at a starting dose of 0.8 mg/kg every two weeks or oral phosphate (recommended dose 20-60 mg/kg/day) and active vitamin D (recommended doses calcitriol 20-30 ng/kg/day or alfacalcidol 40-60 ng/kg/day). Patients randomized to active control received a mean oral phosphate dose of approximately 41 mg/kg/day (range 18 to 110 mg/kg/day) at Week 40 and approximately 46 mg/kg/day (range 18 mg/kg/day to 166 mg/kg/day) at Week 64. They also received either a mean oral calcitriol dose of 26 ng/kg/day at Week 40 and 27 ng/kg/day at Week 64 or a therapeutically equivalent amount of alfacalcidol. Eight patients in the CRYSVITA arm titrated up to 1.2 mg/kg based on serum phosphorus measurements. All patients completed at least 64 weeks on study.

Serum Phosphorus

In Study 1, CRYSVITA increased mean (SD) serum phosphorus levels from 2.4 (0.24) mg/dL at baseline to 3.3 (0.43) mg/dL at Week 40 and to 3.3 (0.42) mg/dL at Week 64. In the active control group, mean (SD) serum phosphorus concentrations increased from 2.3 (0.26) mg/dL at baseline to 2.5 (0.34) mg/dL at Week 40 and to 2.5 (0.39) mg/dL at Week 64. The renal phosphate reabsorptive capacity as assessed by TmP/GFR increased in the CRYSVITA-treated patients from a mean (SD) of 2.2 (0.37) mg/dL at baseline to 3.4 (0.67) mg/dL and 3.3 (0.65) mg/dL at Week 40 and Week 64, respectively. In the active control group, mean (SD) TmP/GFR decreased from 2.0 (0.33) mg/dL at Baseline to 1.8 (0.35) mg/dL at Week 40, and remained below baseline at Week 64 at 1.9 (0.49) mg/dL.

Figure 1: Serum Phosphorus Concentration and Change from Baseline (mg/dL) (Mean ± SD) by Treatment Group in Children 1-12 Years in Study 1

The dotted line represents the lower limit of normal (3.2 mg/dL) for patients in Study 1.

Radiographic Evaluation of Rickets

Radiographs were examined to assess XLH-related rickets using the 10-point Thacher Rickets Severity Score (RSS) and the 7-point Radiographic Global Impression of Change (RGI-C). The RSS score is assigned based on images of the wrist and knee from a single timepoint, with higher scores indicating greater rickets severity. The RGI-C score is assigned based on side-by-side comparisons of wrist and knee radiographs from two timepoints, with higher scores indicating greater improvement in radiographic evidence of rickets. A RGI-C score of +2.0 was defined as radiographic evidence of substantial healing.

In Study 1, baseline mean (SD) total RSS was 3.2 (0.98) in the CRYSVITA group and 3.2 (1.14) in the active control group. After 40 weeks of treatment with CRYSVITA, mean total RSS decreased from 3.2 to 1.1 (0.72) and from 3.2 to 2.5 (1.09) in the active control group. LS mean (SE) RGI-C Global score was +1.9 (0.11) in the CRYSVITA group and +0.8 (0.11) in the active control group at Week 40 (see Table 10). At Week 40, 21 of the 29 patients in the CRYSVITA group and 2 of the 32 patients in the active control arm achieved a RGI-C global score ≥ +2.0. These findings were maintained at Week 64 as shown in Table 10.

Table 10: Rickets Response in Children 1-12 Years Receiving CRYSVITA Every 2 Weeks in Study 1
Endpoint Timepoint | CRYSVITA Every 2 Weeks (N=29) | Active Control (N=32)
RSS Total Score
Baseline Mean (SD) | 3.2 (0.98) | 3.2 (1.14)
LS Mean change from baseline in total score [The estimates of LS mean and 95% CI for Week 40 are from an ANCOVA model accounting for treatment group, baseline RSS and baseline age stratification factor; the estimates for Week 64 are from a generalized estimating equation (GEE) model accounting for treatment group, visit, treatment by visit interaction, baseline RSS and baseline age stratification factor.] (reduction indicates improvement) with 95% CI
Week 40 | -2.0 (-2.33, -1.75) | -0.7 (-0.98, -0.43)
Week 64 | -2.2 (-2.46, -2.00) | -1.0 (-1.31, -0.72)
RGI-C Global Score [RGI-C at Week 40 is the primary endpoint of Study 1]
LS Mean score (positive indicates healing) with 95% CI
Week 40 | +1.9 (+1.70, +2.14) | +0.8 (+0.56, +0.99)
Week 64 | +2.06 (+1.91, +2.20) | +1.03 (+0.77, +1.30)

Lower Extremity Skeletal Abnormality

In Study 1, lower extremity skeletal abnormalities were assessed by RGI-C in standing long leg radiographs. At Week 64, the CRYSVITA group maintained greater improvement compared with the active control group (LS mean [SE]: +1.25 [0.17] versus +0.29 [0.12]; difference of +0.97 (95% CI: +0.57, +1.37, GEE model)).

Serum Alkaline Phosphatase Activity

For Study 1, mean (SD) serum total alkaline phosphatase activity decreased from 511 (125) at baseline to 337 (86) U/L in the CRYSVITA group (mean change: -33%) and from 523 (154) at baseline to 495 (182) U/L in the active control group (mean change: -5%) at Week 64.

Growth

In Study 1, CRYSVITA treatment for 64 weeks increased standing mean (SD) height Z score from -2.32 (1.17) at baseline to -2.11 (1.11) at Week 64 (LS mean change (SE) of +0.17 (0.07)). In the active control group, mean (SD) height Z score increased from -2.05 (0.87) at baseline to -2.03 (0.83) at Week 64 (LS mean (SE) change of +0.02 (0.04)). The difference between the treatment groups at Week 64 was +0.14 (95% CI: 0.00, +0.29).

Study 2 (NCT 02163577) is a randomized, open-label study in 52 prepubescent XLH patients, 5 to 12 years old, which compared treatment with CRYSVITA administered every 2 weeks versus every 4 weeks. Following an initial 16-week dose titration phase, patients completed 48-weeks of treatment with CRYSVITA every 2 weeks. All 52 patients completed at least 64 weeks on study; no patient discontinued. Burosumab-twza dose was adjusted to target a fasting serum phosphorus concentration of 3.5 to 5.0 mg/dL based on the fasting phosphorus level the day of dosing. Twenty-six of 52 patients received CRYSVITA every two weeks up to a maximum dose of 2 mg/kg. The average dose was 0.73 mg/kg (range: 0.3, 1.5) at Week 16, 0.98 mg/kg (range: 0.4, 2.0) at Week 40 and 1.04 mg/kg (range: 0.4, 2.0) at Week 60. The remaining 26 patients received CRYSVITA every four weeks. At study entry, the mean age of patients was 8.5 years and 46% were male. Ninety-six percent had received oral phosphate and active vitamin D analogs for a mean (SD) duration of 7 (2.4) years. Oral phosphate and active vitamin D analogs were discontinued prior to study enrollment. Ninety-four percent of patients had radiographic evidence of rickets at baseline.

Study 3 (NCT 02750618) is a 64-week open-label study in 13 pediatric XLH patients, 1 to 4 years old. Patients received CRYSVITA at a dose of 0.8 mg/kg every two weeks with 3 patients titrating up to 1.2 mg/kg based on serum phosphorus measurements. All patients completed at least 40 weeks on study; no patients discontinued. At study entry, the mean age of patients was 2.9 years and 69% were male. All patients had radiographic evidence of rickets at baseline and 12 patients had received oral phosphate and active vitamin D analogs for a mean (SD) duration of 16.7 (14.4) months. Oral phosphate and active vitamin D analogs were discontinued prior to study enrollment.

Serum Phosphorus

In Study 2, CRYSVITA increased mean (SD) serum phosphorus levels from 2.4 (0.40) at baseline to 3.3 (0.40) and 3.4 (0.45) mg/dL at Week 40 and Week 64 in the patients who received CRYSVITA every 2 weeks. The ratio of renal tubular maximum reabsorption rate of phosphate to glomerular filtration rate (TmP/GFR) increased in these patients from mean (SD) of 2.2 (0.49) at baseline to 3.3 (0.60) and 3.4 (0.53) mg/dL at Week 40 and Week 64.

In Study 3, CRYSVITA increased mean (SD) serum phosphorus levels from 2.5 (0.28) mg/dL at baseline to 3.5 (0.49) mg/dL at Week 40.

Radiographic Evaluation of Rickets

In Study 2, baseline mean (SD) RSS total score was 1.9 (1.17) in patients receiving CRYSVITA every two weeks. After 40 weeks of treatment with CRYSVITA, mean total RSS decreased from 1.9 to 0.8 (see Table 11). After 40 weeks of treatment with CRYSVITA, the mean RGI-C Global score was +1.7 in patients receiving CRYSVITA every two weeks. Eighteen out of 26 patients achieved an RGI-C score of ≥ +2.0. These findings were maintained at Week 64 as shown in Table 11.

In Study 3, baseline mean (SD) total RSS was 2.9 (1.37) in 13 patients. After 40 weeks of treatment with CRYSVITA, mean total RSS decreased from 2.9 to 1.2 and the mean (SE) RGI-C Global score was +2.3 (0.08) (see Table 11). All 13 patients achieved a RGI-C global score ≥ +2.0.

Table 11: Rickets Response in Children 1-12 Years Receiving CRYSVITA Every 2 Weeks in Study 2 and Study 3
Endpoint Timepoint | CRYSVITA Every 2 Weeks
Endpoint Timepoint | Study 2 [The estimates of LS mean and 95% CI are from a generalized estimating equation (GEE) model accounting for regimen, visit, regimen by visit interaction, baseline RSS for study 2.] (N=26) | Study 3 [The estimates of LS mean and 95% CI for Week 40 are from an ANCOVA model accounting for age and baseline RSS for study 3.] (N=13)
RSS Total Score
Baseline Mean (SD) | 1.9 (1.17) | 2.9 (1.37)
LS Mean change from baseline in total score (reduction indicates improvement) with 95% CI
Week 40 | -1.1 (-1.28, -0.85) | -1.7 (-2.03, -1.44)
Week 64 | -1.0 (-1.2, -0.79)
RGI-C Global Score
LS Mean score (positive indicates healing) with 95% CI
Week 40 | +1.7 (+1.48, +1.84) | +2.3 (+2.16, +2.51)
Week 64 | +1.6 (+1.34, +1.78)

Lower Extremity Skeletal Abnormality

In Study 3, the mean (SE) change in lower limb deformity as assessed by RGI-C, using standing long leg radiographs, was +1.3 (0.14) at Week 40.

Serum Alkaline Phosphatase Activity

For Study 2, mean (SD) serum total alkaline phosphatase activity was 462 (110) U/L at baseline and decreased to 354 (73) U/L at Week 64 (-23%) in the patients who received CRYSVITA every 2 weeks.

For Study 3, mean (SD) serum total alkaline phosphatase activity was 549 (194) U/L at baseline and decreased to 335 (88) U/L at Week 40 (mean change: -36%).

Growth

In Study 2, CRYSVITA treatment for 64 weeks increased standing mean (SD) height Z score from -1.72 (1.03) at baseline to -1.54 (1.13) in the patients who received CRYSVITA every two weeks (LS mean change of +0.19 (95% CI: 0.09 to 0.29).

14.2 Adult X-linked Hypophosphatemia

Study 4 (NCT 02526160) is a randomized, double-blind, placebo-controlled study in 134 adult XLH patients. The study comprises a 24-week placebo-controlled treatment phase followed by a 24-week open-label treatment period in which all patients received CRYSVITA. CRYSVITA was administered at a dose of 1 mg/kg every 4 weeks. At study entry, the mean age of patients was 40 years (range 19 to 66 years) and 35% were male. All patients had skeletal pain associated with XLH/osteomalacia at baseline. The baseline mean (SD) serum phosphorus concentration was below the lower limit of normal at 1.98 (0.31) mg/dL. Oral phosphate and active vitamin D analogs were not allowed during the study. Out of the 134 patients enrolled in the study, one patient in the CRYSVITA group discontinued treatment during the 24-week placebo-controlled treatment period, and 7 patients discontinued CRYSVITA during the open-label treatment period.

Study 5 (NCT 02537431) is a 48-week, open-label, single-arm study in 14 adult XLH patients to assess the effects of CRYSVITA on improvement of osteomalacia as determined by histologic and histomorphometric evaluation of iliac crest bone biopsies. Patients received 1 mg/kg CRYSVITA every four weeks. At study entry, the mean age of patients was 40 years (range 25 to 52 years) and 43% were male. Oral phosphate and active vitamin D analogs were not allowed during the study.

Serum Phosphorus

In Study 4 at baseline, mean (SD) serum phosphorus was 1.9 (0.32) and 2.0 (0.30) mg/dL in the placebo and CRYSVITA groups respectively. During the initial 24-week double-blind, placebo-controlled period, mean (SD) serum phosphorus across the midpoints of dose intervals (2 weeks post dose) was 2.1 (0.30) and 3.2 (0.53) mg/dL in the placebo and CRYSVITA groups, and mean (SD) serum phosphorus across the ends of dose intervals was 2.0 (0.30) and 2.7 (0.45) mg/dL in the placebo and CRYSVITA groups.

A total of 94% of patients treated with CRYSVITA achieved a serum phosphorus level above the lower limit of normal (LLN) compared to 8% in the placebo group through Week 24 (see Table 12).

Table 12: Proportion of Adult Patients Achieving Mean Serum Phosphorus Levels Above the LLN at the Midpoint of the Dose Interval During the 24-Week Placebo-Controlled Period of Study 4
 | Placebo (N = 66) | CRYSVITA (N = 68)
Achieved Mean Serum Phosphorus > LLN Across Midpoints of Dose Intervals Through Week 24 - n (%) | 5 (8%) | 64 (94%)
95% CI | (3.3, 16.5) | (85.8, 97.7)
p-value [P-value is from Cochran-Mantel-Haenszel (CMH) testing for association between achieving the primary endpoint and treatment group, adjusting for randomization stratifications.] |  | < 0.0001
The 95% CIs are calculated using the Wilson score method.

During the open-label treatment period, serum phosphorus was maintained during continued CRYSVITA therapy, with no evidence of loss of effect through Week 48.

Figure 2: Mean (± SD) Serum Phosphorus Peak Concentrations (mg/dL) in Study 4 [Placebo subjects cross over to receive open-label CRYSVITA treatment at Week 24] , [The dotted lines represent the upper limit of normal (4.5 mg/dL) and lower limit of normal (2.5 mg/dL) for patients in Study 4]

At baseline, the mean (SD) ratio of renal tubular maximum reabsorption rate of phosphate to glomerular filtration rate (TmP/GFR) was 1.60 (0.37) and 1.68 (0.40) mg/dL in the placebo and CRYSVITA groups respectively. At Week 22 (midpoint of a dose interval), mean (SD) TmP/GFR was 1.69 (0.37) and 2.73 (0.75) mg/dL in the placebo and CRYSVITA groups. At Week 24 (end of a dose interval), mean (SD) TmP/GFR was 1.73 (0.42) and 2.21 (0.48) mg/dL in the placebo and CRYSVITA groups. During the open-label treatment period, TmP/GFR remained stable during continued CRYSVITA therapy through Week 48.

Radiographic Evaluation of Osteomalacia

In Study 4, a skeletal survey was conducted at baseline to identify osteomalacia-related fractures and pseudofractures. Osteomalacia-related fractures are defined as atraumatic lucencies extending across both bone cortices and pseudofractures are defined as atraumatic lucencies extending across one cortex. There were 52% of patients who had either active (unhealed) fractures (12%) or active pseudofractures (47%) at baseline. The active fractures and pseudofractures were predominantly located in the femurs, tibia/fibula, and metatarsals of the feet. Assessment of these active fracture/pseudofracture sites at Week 24 demonstrated a higher rate of complete healing in the CRYSVITA group compared to placebo as shown in Table 13. During the double-blind, placebo-controlled treatment period through Week 24, a total of 6 new fractures or pseudofractures appeared in 68 patients receiving CRYSVITA, compared to 8 new abnormalities in 66 patients receiving placebo (see Table 13).

Table 13: Comparison of Fracture Healing with CRYSVITA vs Placebo in Study 4 Double Blind Period
 | Active Fractures |  | Active Pseudofractures |  | Total Fractures
 | Placebo n (%) | CRYSVITA n (%) | Placebo n (%) | CRYSVITA n (%) | Placebo n (%) | CRYSVITA n (%)
No. of fractures at baseline | 13 | 14 | 78 | 51 | 91 | 65
Healed at Week 24 | 0 (0%) | 7 (50%) | 7 (9%) | 21 (41%) | 7 (8%) | 28 (43%)

During the open-label treatment period, the patients who continued receiving CRYSVITA showed continued healing of fractures at Week 48 [active fractures (n = 8, 57%), active pseudofractures (n = 33, 65%)]. In the 'placebo to CRYSVITA' group, fracture healing at Week 48 was observed for active fractures (n = 6, 46%), and active pseudofractures (n = 26, 33%).

Patient Reported Outcomes

Study 4 evaluated patient-reported XLH-related symptoms (pain, joint stiffness, and physical function).

At 24 weeks, the CRYSVITA arm showed a mean improvement from baseline (-7.9) compared to the placebo arm (+0.3) in the stiffness severity score (range 0 to 100; lower scores are reflective of symptom improvement).

At 24 weeks, no significant difference between CRYSVITA and placebo was demonstrated in patient-reported pain intensity or physical function score.

Bone Histomorphometry

In Study 5, after 48 weeks of treatment, healing of osteomalacia was observed in ten patients as demonstrated by decreases in Osteoid volume/Bone volume (OV/BV) from a mean (SD) score of 26% (12.4) at baseline to 11% (6.5), a change of -57%. Osteoid thickness (O.Th) declined in eleven patients from a mean (SD) of 17 (4.1) micrometers to 12 (3.1) micrometers, a change of -33%. Mineralization lag time (MLt) declined in 6 patients from a mean (SD) of 594 (675) days to 156 (77) days, a mean change of -74%.

14.3 Tumor-induced Osteomalacia

CRYSVITA has been evaluated in two studies enrolling a total of 27 patients with TIO.

Study 6 (NCT 02304367) is a single-arm open-label study that enrolled 14 adult patients with a confirmed diagnosis of FGF23-related hypophosphatemia produced by an underlying tumor that was not amenable to surgical excision or could not be located. Of the 14 TIO patients enrolled in Study 6, eight were male, and patients ranged from 33 years to 68 years of age (Median 59.5 years). Oral phosphate and active vitamin D analogs were discontinued two weeks prior to study enrollment. Patients received CRYSVITA every 4 weeks at a weight based starting dose of 0.3 mg/kg that was titrated to achieve a fasting serum phosphorus level of 2.5 to 4.0 mg/dL. The mean dose was 0.83 mg/kg at Week 20, 0.87 mg/kg at Week 48, 0.77 mg/kg at Week 96 and 0.71 mg/kg at Week 144.

Study 7 (NCT 02722798) is a single-arm open-label study. In Study 7, 13 adult patients with a confirmed diagnosis of TIO received CRYSVITA. Of the 13 TIO patients who received treatment in Study 7, six were male, and patients ranged from 41 years to 73 years of age (Median 58.0 years). Oral phosphate and active vitamin D analogs were discontinued two weeks prior to study enrollment. Patients received CRYSVITA every 4 weeks at a weight based starting dose of 0.3 mg/kg that was titrated to achieve a fasting serum phosphorus level of 2.5 to 4.0 mg/dL. The mean (SD) dose was 0.91 (0.59) mg/kg at Week 48, and 0.96 (0.70) mg/kg at Week 88.

Serum Phosphorus

In Study 6, CRYSVITA increased mean (SD) serum phosphorus levels from 1.60 (0.47) mg/dL at baseline to 2.64 (0.76) mg/dL averaged across the midpoint of dose intervals through Week 24 with 50% of patients (7/14) achieving a mean serum phosphorus level above the LLN averaged across the midpoint of dose intervals through Week 24. Increase in the mean serum phosphorus concentrations was sustained near or above the LLN through Week 144 (Figure 3). The ratio of renal tubular maximum reabsorption rate of phosphate to glomerular filtration rate (TmP/GFR) increased in these patients from a mean (SD) of 1.12 (0.54) mg/dL at baseline to 2.12 (0.64) mg/dL at Week 48, and remained stable through Week 144.

Figure 3: Serum Phosphorus Concentration and Change from Baseline in Study 6 (mg/dL)

The dotted line represents the lower limit of normal (2.5 mg/dL) for patients in study 6.

In Study 7, CRYSVITA increased mean (SD) serum phosphorus levels from 1.62 (0.49) mg/dL at baseline to 2.63 (0.87) mg/dL averaged across the midpoint of dose intervals through Week 24 with 69% of patients (9/13) achieving a mean serum phosphorus level above the LLN averaged across the midpoint on dose interval through Week 24. Mean serum phosphorus concentrations were sustained above LLN through Week 88. The renal phosphate reabsorptive capacity, as assessed by TmP/GFR, increased from a mean (SD) of 1.15 (0.43) mg/dL at baseline to 2.30 mg/dL (0.48) mg/dL at Week 48.

Bone Histomorphometry

In Study 6, osteomalacia was present at baseline in nine out of 11 patients with paired bone biopsies, and healing was assessed after 48 weeks of treatment. In these 9 patients with osteomalacia at baseline, OV/BV decreased from a mean (SD) score of 21.2% (19.9) at baseline to 13.9% (16.7), a change of -34%. O.Th declined from a mean (SD) of 18.9 (11.9) micrometers to 12.1 (10.1) micrometers, a change of -36%. MLt declined in 3 patients from a mean (SD) of 667 (414) days to 331 (396) days, a change of -50%.

In Study 7, osteomalacia was present at baseline in all 3 patients with paired bone biopsies, and healing was assessed after 48 weeks of treatment. In these 3 patients, OV/BV decreased from a mean (SD) score of 14.0% (15.2) at baseline to 9.2% (5.5), a change of -34%. O.Th declined from a mean (SD) of 16.0 (13.7) micrometers to 13.5 (7.1) micrometers, a change of -16%.

Radiographic Evaluation of Osteomalacia

In Study 6, 99mtechnetium-labelled whole body bone scans were performed at baseline and subsequent timepoints during the study on all 14 patients. Bone scans allow for assessment of sites of increased tracer uptake in a wide range of bone conditions, including osteomalacia. In patients with TIO, increased tracer uptake on bone scan is presumed to be nontraumatic fractures and pseudofractures. At baseline, all patients had areas of tracer uptake with a total of 249 bone abnormalities across 14 patients. The number of areas of tracer uptake decreased from Week 48 through Week 144, suggesting healing of the bone abnormalities.

16 HOW SUPPLIED/STORAGE AND HANDLING

CRYSVITA (burosumab-twza) injection for subcutaneous administration is supplied as a sterile, preservative-free, clear to slightly opalescent and colorless to pale brown-yellow solution. The product is available as one single-dose vial per carton in the following strengths:

10 mg/mL (NDC# 42747-102-01)

20 mg/mL (NDC# 42747-203-01)

30 mg/mL (NDC# 42747-304-01)

STORAGE AND HANDLING

CRYSVITA vials must be stored in the original carton until the time of use under refrigerated conditions at 36°F to 46°F (2°C to 8°C). Keep CRYSVITA vial in the original carton to protect from light until time of use.

Do not freeze or shake CRYSVITA.

Do not use CRYSVITA beyond the expiration date stamped on the carton.

CRYSVITA vials are single-dose only. Discard any unused product.

17 PATIENT COUNSELING INFORMATION

Drug Interactions

Advise patients not to use any oral phosphate and/or active vitamin D analog products [see Contraindications (4)].

Hypersensitivity Reactions

Advise patients that CRYSVITA may cause hypersensitivity events such as rash, injection site rash and urticaria. Instruct the patients to contact their physician if such reactions occur [see Adverse Reactions (6.1)].

Injection Site Reactions

Inform patients that injection site reactions (e.g. erythema, rash, swelling, bruising, pain, pruritus, urticaria, and hematoma) have occurred at the site of CRYSVITA injection. Instruct the patients to contact their physician if such reactions occur [see Adverse Reactions (6.1)].

Restless Legs Syndrome

Advise patients that CRYSVITA can induce RLS or worsen the symptoms of existing RLS. Instruct the patients to contact their physician if such a reaction occurs [see Adverse Reactions (6.1)].

Pregnancy

Report pregnancies to the Kyowa Kirin, Inc. Adverse Event reporting line at 1-844-768-3544 [see Use in Specific Populations (8.1)].

Manufactured by:
Kyowa Kirin, Inc.
Princeton, NJ 08540
U.S. License No. 2077

PRINCIPAL DISPLAY PANEL - 10 mg/mL Vial

NDC 42747-102-01

CRYSViTA®
(burosumab-twza)

Injection

10 mg/mL

1 mL single-dose vial

Kyowa Kirin, Inc.

U.S. License No. 2077

PRINCIPAL DISPLAY PANEL - 10 mg/mL Vial Carton

NDC 42747-102-01

CRYSViTA®
(burosumab-twza)

Injection

10 mg/mL

For Subcutaneous Use Only

Single-Dose Vial

Discard Unused Portion

Rx only
1 vial

PRINCIPAL DISPLAY PANEL - 20 mg/mL Vial

NDC 42747-203-01

CRYSViTA®
(burosumab-twza)

Injection

20 mg/mL

1 mL single-dose vial

Kyowa Kirin, Inc.

U.S. License No. 2077

PRINCIPAL DISPLAY PANEL - 20 mg/mL Vial Carton

NDC 42747-203-01

CRYSViTA®
(burosumab-twza)

Injection

20 mg/mL

For Subcutaneous Use Only

Single-Dose Vial

Discard Unused Portion

Rx only
1 vial

PRINCIPAL DISPLAY PANEL - 30 mg/mL Vial

NDC 42747-304-01

CRYSViTA®
(burosumab-twza)

Injection

30 mg/mL

1 mL single-dose vial

Kyowa Kirin, Inc.

U.S. License No. 2077

PRINCIPAL DISPLAY PANEL - 30 mg/mL Vial Carton

NDC 42747-304-01

CRYSViTA®
(burosumab-twza)

Injection

30 mg/mL

For Subcutaneous Use Only

Single-Dose Vial

Discard Unused Portion

Rx only
1 vial